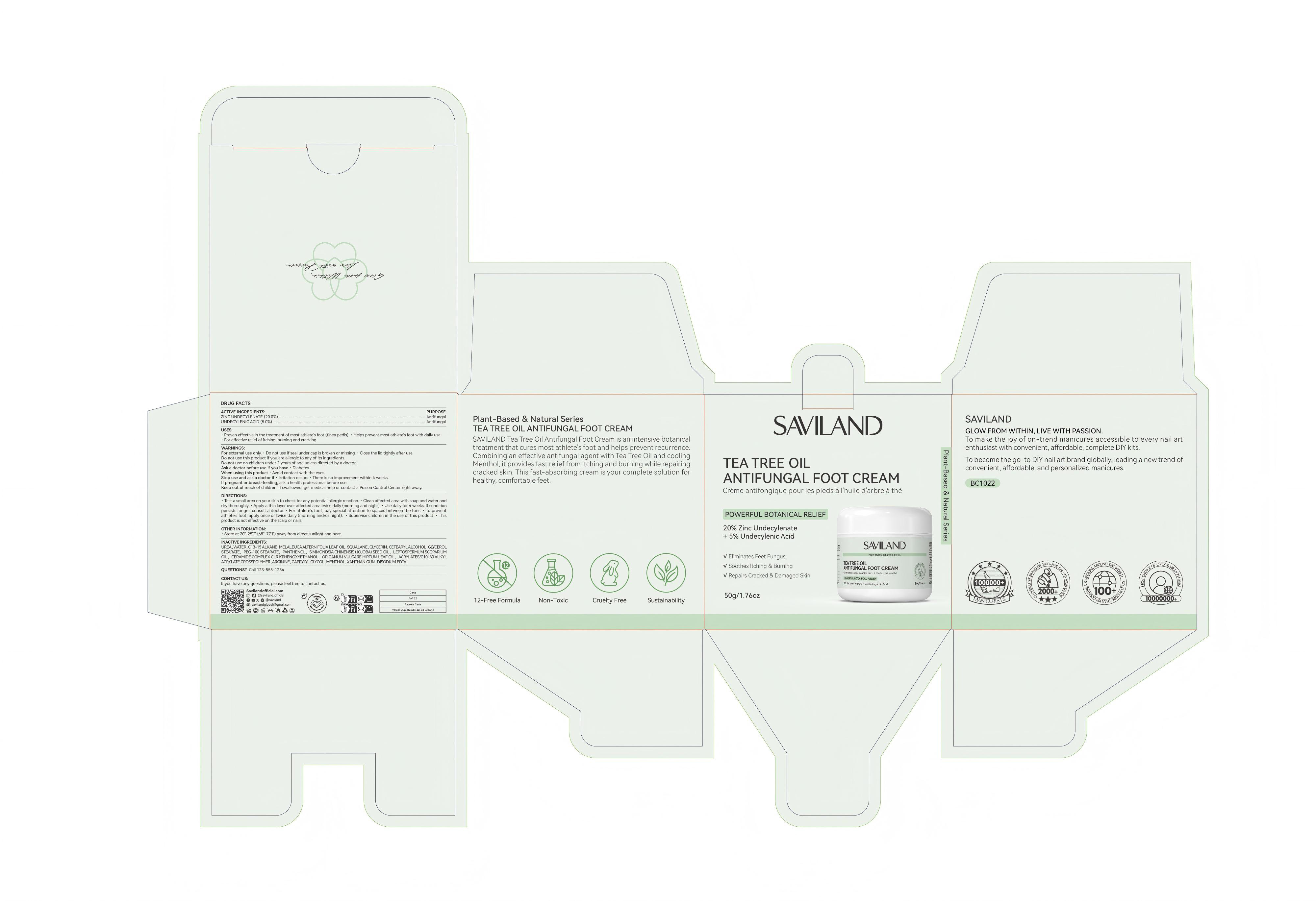 DRUG LABEL: Tea Tree Oil Antifungal Foot Cream
NDC: 85966-007 | Form: CREAM
Manufacturer: GUANGZHOU SAWEILAN IMPORT & EXPORT TRADING CO., LTD
Category: otc | Type: HUMAN OTC DRUG LABEL
Date: 20250928

ACTIVE INGREDIENTS: ZINC UNDECYLENATE 20 g/100 g; UNDECYLENIC ACID 5 g/100 g
INACTIVE INGREDIENTS: UREA; SQUALANE; GLYCERIN; GLYCERYL STEARATE; PEG-100 STEARATE; C13-15 ALKANE; WATER; MELALEUCA ALTERNIFOLIA (TEA TREE) LEAF OIL; SIMMONDSIA CHINENSIS (JOJOBA) SEED OIL; PANTHENOL; LEPTOSPERMUM SCOPARIUM BRANCH/LEAF OIL; SOY SPHINGOLIPIDS; PHENOXYETHANOL; EDETATE DISODIUM; ORIGANUM VULGARE LEAF OIL; CETEARYL ALCOHOL; ARGININE; CAPRYLYL GLYCOL; MENTHOL; ACRYLATES/C10-30 ALKYL ACRYLATE CROSSPOLYMER (60000 MPA.S); XANTHAN GUM

85966-007 Tea Tree Oil Antifungal Foot Cream

ACTIVE INGREDIENT

ZINC UNDECYLENATE 20%
UNDECYLENIC ACID 5%

PURPOSE

Antifungal

INDICATIONS AND USAGE

Proven effective in the treatment of most athlete's foot (tinea pedis) . Helps prevent most athlete's foot with daily use
For effective relief of itching, burning and cracking.

WARNINGS

For external use only.

Do not use if seal under cap is broken or missing. Close the lid tightly after use.
Do not use this product if you are allergic to any of its ingredients.
Do not use on children under 2 years of age unless directed by a doctor.

Ask a doctor before use if you have .Diabetes.
When using this product . Avoid contact with the eyes.
If pregnant or breast-feeding, ask a health professional before use.

Stop use and ask a doctor if , lrritation occurs There is no improvement within 4 weeks.

Keep out of reach of children. if swallowed, get medical help or contact a Poison Control Center right away.

DOSAGE AND ADMINISTRATION

Test a small area on your skin to check for any potential allergic reaction. . Clean affected area with soap and water anddry thoroughly, · Apply a thin layer over affected area twice daily (morning and night). . Use daily for 4 weeks. if conditionoersists longer, consult a doctor. . For athlete's foot, pay special attention to spaces between the toes, . To preventathlete's foot, apply once or twice daily (morning and/or night). ’ Supervise children in the use of this product, . Thisproduct is not effective on the scalp or nails.

INACTIVE INGREDIENT

UREA
WATER
C13-15 ALKANE
MELALEUCA ALTERNIFOLIA LEAF OIL
SQUALANE
GLYCERIN
CetearyAlcohol/CETEARYL ALCOHOL
GLYCEROL STEARATE
PEG-100 STEARATE
PANTHENOL
SIMMONDSIA CHINENSIS (JOJOBA) SEED OIL
LEPTOSPERMUM SCOPARIUM OIL
CERAMIDE COMPLEX CLR K
PHENOXYETHANOL
ORIGANUM VULGARE HIRTUM LEAF OIL
ACRYLATES/C10-30 ALKYL ACRYLATE CROSSPOLYMER
ARGININE
CAPRYLYL GLYCOL
MENTHOL
XANTHAN GUM
DISODIUM EDTA